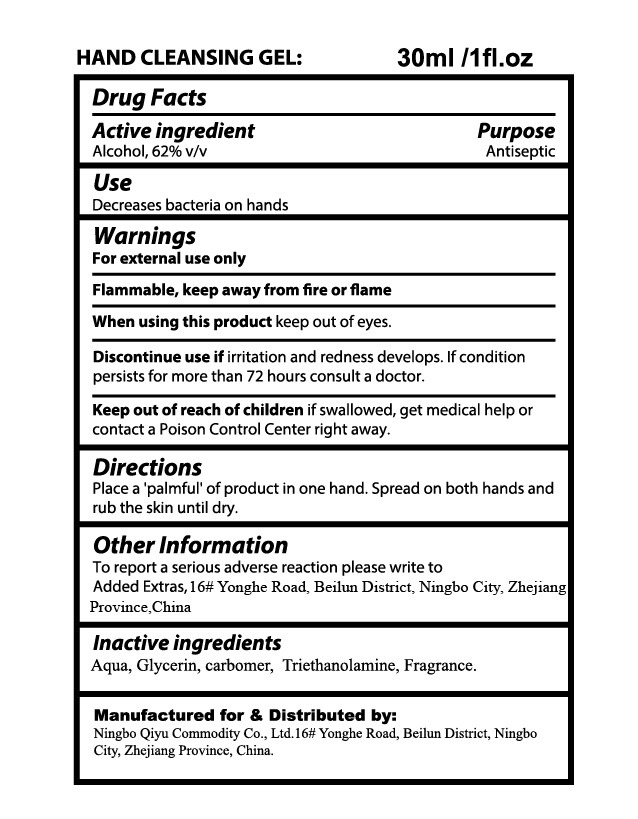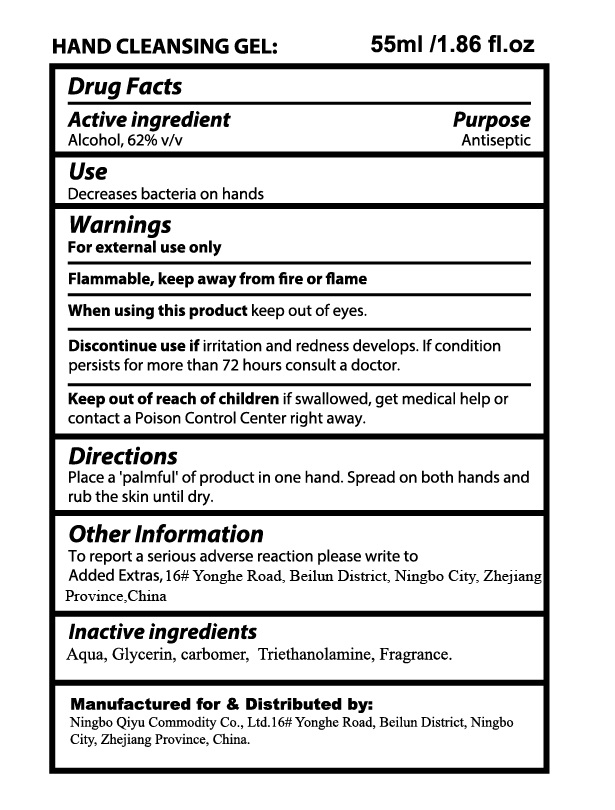 DRUG LABEL: Disposable Hand Sanitizing
NDC: 76562-005 | Form: GEL
Manufacturer: Ningbo Qiyu Commodity Co., Ltd.
Category: otc | Type: HUMAN OTC DRUG LABEL
Date: 20200616

ACTIVE INGREDIENTS: ALCOHOL 0.62 mL/1 mL
INACTIVE INGREDIENTS: WATER; GLYCERIN; CARBOMER HOMOPOLYMER, UNSPECIFIED TYPE; TROLAMINE

Disposable Hand Sanitizing Gel

Active ingredient

Alcohol, 62% v/v

Purpose

Antiseptic

Use

Decrease bacteria on hands

Warnings

For external use only

Flammable, keep away from fire or flame

When using this product

keep out of eyes.

Discontinue use if

irritation and redness develops. If condition persists for more than 72 hours consult a doctor.

Keep out of reach of children

if swallowed, get medical help or contact a Poison Control Center right away.

Directions

Place a 'palmful of product in one hand. Spread on both hands and rub the skin until dry.

Other Information

To report a serious adverse reaction please write to Added Extras,16# Yonghe Road, Beilun District, Ningbo City, Zhejiang Province,China

Inactive ingredients

Aqua, Glycerin, carbomer, Triethanolamine, Fragrance.